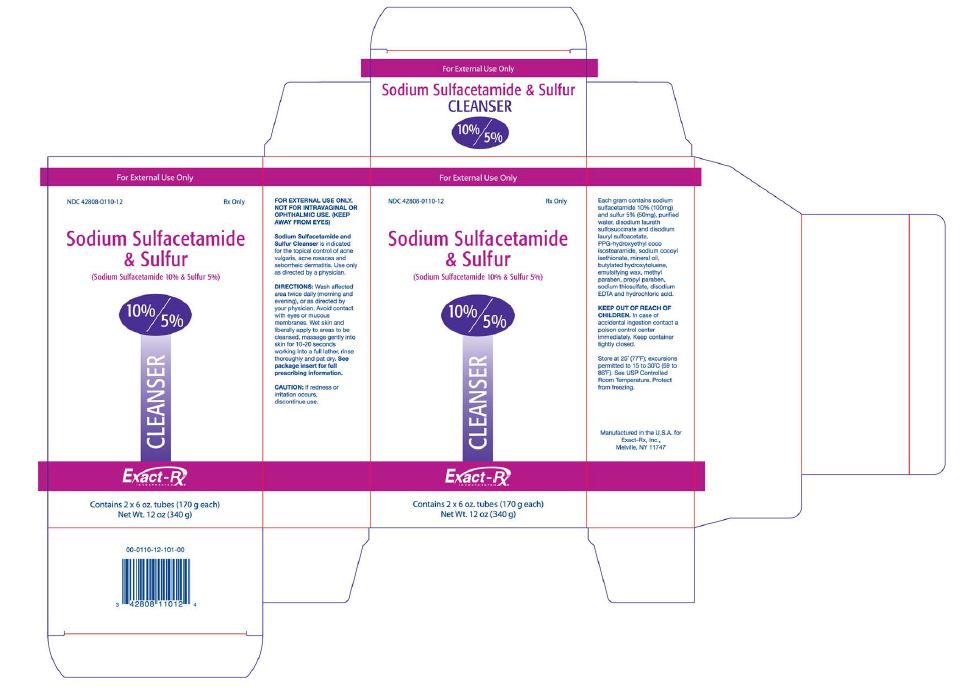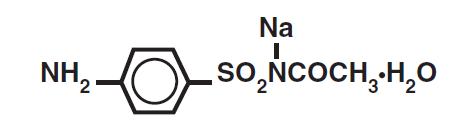 DRUG LABEL: SODIUM SULFACETAMIDE, SULFUR
NDC: 42808-110 | Form: SOLUTION
Manufacturer: Exact-Rx, Inc.
Category: prescription | Type: HUMAN PRESCRIPTION DRUG LABEL
Date: 20110801

ACTIVE INGREDIENTS: SULFACETAMIDE SODIUM 100 mg/1 g; SULFUR 50 mg/1 g
INACTIVE INGREDIENTS: WATER; DISODIUM LAURETH SULFOSUCCINATE; SODIUM LAURYL SULFOACETATE; SODIUM COCOYL ISETHIONATE; MINERAL OIL; BUTYLATED HYDROXYTOLUENE; METHYLPARABEN; PROPYLPARABEN; SODIUM THIOSULFATE; EDETATE DISODIUM; HYDROCHLORIC ACID; YELLOW WAX

Sodium Sulfacetamide 10% and Sulfur 5% Cleanser
Rx only

DESCRIPTION

DESCRIPTION: Sodium sulfacetamide is a sulfonamide with antibacterial activity while sulfur acts as a keratolytic agent. Chemically sodium sulfacetamide is N-[(4-aminophenyl)sulfonyl]-acetamide, monosodium salt, monohydrate. The structural formula is:

Each gram contains sodium sulfacetamide 10% (100 mg) and sulfur 5% (50 mg), purified water, disodium laureth sulfosuccinate and disodium lauryl sulfoacetate, PPG-hydroxyethyl coco isostearamide, sodium cocoyl isethionate, mineral oil, butylated hydroxytoluene, emulsifying wax, methyl paraben, propyl paraben, sodium thiosulfate, disodium EDTA and hydrochloric acid.

CLINICAL PHARMACOLOGY

CLINICAL PHARMACOLOGY: The most widely accepted mechanism of action of sulfonamides is the Woods-Fildes theory which is based on the fact that sulfonamides act as competitive antagonists to para-aminobenzoic acid (PABA), an essential component for bacterial growth. While absorption through intact skin has not been determined, sodium sulfacetamide is readily absorbed from the gastrointestinal tract when taken orally and excreted in the urine, largely unchanged. The biological half-life has variously been reported as 7 to 12.8 hours. The exact mode of action of sulfur in the treatment of acne is unknown, but it has been reported that it inhibits the growth of Propionibacterium acnes and the formation of free fatty acids.

INDICATIONS AND USAGE

INDICATIONS: Sodium Sulfacetamide 10% & Sulfur 5% Cleanser is indicated in the topical control of acne vulgaris, acne rosacea and seborrheic dermatitis.

CONTRAINDICATIONS

CONTRAINDICATIONS: Sodium Sulfacetamide 10% & Sulfur 5% Cleanser is contraindicated for use by patients having known hypersensitivity to sulfonamides, sulfur or any other component of this preparation. Sodium Sulfacetamide 10% & Sulfur 5% Cleanser is not to be used by patients with kidney disease.

WARNINGS

WARNINGS: Although it is rare, sensitivity to sodium sulfacetamide may occur. Therefore, caution and careful supervision should be observed when prescribing this drug for patients who may be prone to hypersensitivity to topical sulfonamides. Systemic toxic reactions such as agranulocytosis, acute hemolytic anemia, purpura hemorrhagica, drug fever, jaundice, and contact dermatitis indicate hypersensitivity to sulfonamides. Particular caution should be employed if areas of denuded or abraded skin are involved.

FOR EXTERNAL USE ONLY. Keep away from eyes.

KEEP OUT OF REACH OF CHILDREN.

In case of accidental ingestion contact a poison control center immediately. Keep container tightly closed.

WARNINGS AND PRECAUTIONS

PRECAUTIONS: General: If irritation develops, use of the product should be discontinued and appropriate therapy instituted. Patients should be carefully observed for possible local irritation or sensitization during long-term therapy. The object of this therapy is to achieve desquamation without irritation, but sodium sulfacetamide and sulfur can cause reddening and scaling of the epidermis. These side effects are not unusual in the treatment of acne vulgaris, but patients should be cautioned about the possibility.

PATIENT COUNSELING INFORMATION

Information for Patients: Avoid contact with eyes, eyelids, lips and mucous membranes. If accidental contact occurs, rinse with water. If excessive irritation develops, discontinue use and consult your physician.

CARCINOGENESIS AND MUTAGENESIS AND IMPAIRMENT OF FERTILITY

Carcinogenesis, Mutagenesis and Impairment of Fertility: Long-term studies in animals have not been performed to evaluate carcinogenic potential.

PREGNANCY

Pregnancy: Category C. Animal reproduction studies have not been conducted with Sodium Sulfacetamide 10% & Sulfur 5% Cleanser. It is also not known whether Sodium Sulfacetamide 10% & Sulfur 5% Cleanser can cause fetal harm when administered to a pregnant woman or can affect reproduction capacity. Sodium Sulfacetamide 10% & Sulfur 5% Cleanser should be given to a pregnant woman only if clearly needed.

NURSING MOTHERS

Nursing Mothers: It is not known whether sodium sulfacetamide is excreted in the human milk following topical use of Sodium Sulfacetamide 10% & Sulfur 5% Cleanser. However, small amounts of orally administered sulfonamides have milk. In view of this and because many drugs are excreted in human milk, caution should be exercised when Sodium Sulfacetamide 10% & Sulfur 5% Cleanser is administered to a nursing woman.

PEDIATRIC USE

Pediatric Use: Safety and effectiveness in children under the age of 12 years have not been established.

ADVERSE REACTIONS

ADVERSE REACTIONS: Although rare, sodium sulfacetamide may cause local irritation.

Call your doctor for medical advice about side effects.

DOSAGE AND ADMINISTRATION: Wash affected areas once or twice daily, or as directed by your physician. Avoid contact with eyes or mucous membranes. Wet skin and liberally apply to areas to be cleansed, massage gently into skin for 10–20 seconds working into a full lather, rinse thoroughly and pat dry. If drying occurs, it may be controlled by rinsing cleanser off sooner or using less often.

HOW SUPPLIED

HOW SUPPLIED: Sodium Sulfacetamide 10% & Sulfur 5% Cleanser is available in a 6 oz (170 g) tube, NDC 42808-0110-06 and 12 oz carton that contains (2) 6 oz tubes, NDC 42808-0110-12.

STORAGE AND HANDLING

Store at controlled room temperature 15-30°C (59-86°F).

Protect from freezing.

Manufactured in the U.S.A. for Exact-Rx, Inc., Melville, NY 11747

00-0100-99-205-00

Iss:6/11

PACKAGE LABEL - 12 oz (340 g)

For External Use Only

NDC 42808-0110-12 Rx Only

Sodium Sulfacetamide
& Sulfur

(Sodium Sulfacetamide 10% & Sulfur 5%)

10%/5%

CLEANSER

Exact-Rx.
INCORPORATED

Contains 2 x 6 oz. tubes (170 g each)
Net Wt. 12 oz (340 g)